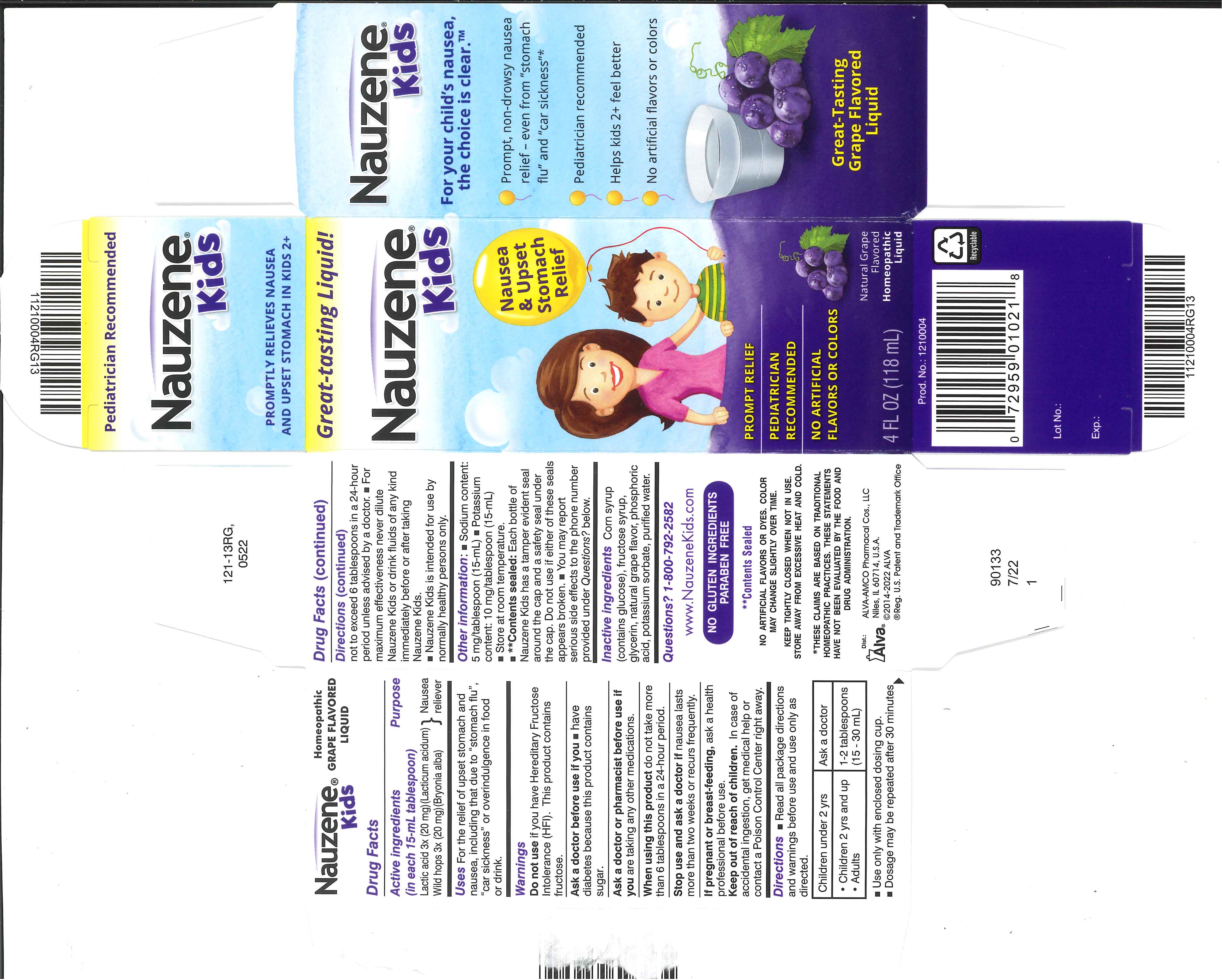 DRUG LABEL: Nauzene Homeopathic
NDC: 52389-621 | Form: LIQUID
Manufacturer: Alva-Amco Pharmacal Companies, Inc.
Category: homeopathic | Type: HUMAN OTC DRUG LABEL
Date: 20230929

ACTIVE INGREDIENTS: BRYONIA ALBA ROOT 3 [hp_X]/15 mL; LACTIC ACID 3 [hp_X]/15 mL
INACTIVE INGREDIENTS: CORN SYRUP; HIGH FRUCTOSE CORN SYRUP; GLYCERIN; PHOSPHORIC ACID; WATER; POTASSIUM SORBATE

Nauzene Homeopathic

Active ingredients (in each 15-mL tablespoon)

Lactic acid 3x (20 mg)(Lacticum acidum)

Wild hops 3x (20 mg)(Bryonia alba)

Purpose

Nausea reliever

Uses

For the relief of upset stomach and nausea, including that due to "stomach flu", "car sickness" or overindulgence in food or drink.

Do not use if you have Hereditary Fructose Intolerance (HFI). This product contains fructose.

Ask a doctor before use if you

- have diabetes because this product contains sugar

Ask a doctor or pharmacist before use if you are taking any other medications.

When using this product do not take more than 6 tablespoons in a 24-hour period.

Stop use and ask a doctor if nausea lasts more than two weeks or recurs frequently.

PREGNANCY OR BREAST FEEDING

If pregnant or breast-feeding, ask a health professional before use.

Keep out of reach of children. In case of accidental ingestion, get medical help or contact a Poison Control Center right away.

Directions

- Read all package directions and warnings before use and use only as directed.

Children under 2 yrs | Ask a doctor
- Children 2 yrs and up - Adults | 1 - 2 tablespoons; (15 - 30 mL)

- Use only with enclosed dosing cup.
- Dosage may be repeated after 30 minutes not to exceed 6 tablespoons in a 24-hour period unless advised by a doctor.
- For maximum effectiveness never dilute Nauzene Kids or drink fluids of any kind immediately before or after taking Nauzene Kids.
- Nauzene Kids is intended for use by normally healthy persons only.

Other information

- Sodium content: 5 mg/tablespoon (15-mL)
- Potassium content: 10 mg/tablespoon (15-mL)
- Store at room temperature.
- **Contents sealed: Each bottle of Nauzene Kids has a tamper evident seal around the cap and a safety seal under the cap. Do not use if either of these seals appears broken.
- You may report serious side effectes to the phone number provided under Questions? below.

Inactive ingredients

Corn syrup (contains glucose), fructose syrup, glycerin, natural grape flavor, phosphoric acid, potassium sorbate, purified water.

Questions? 1-800-792-2582